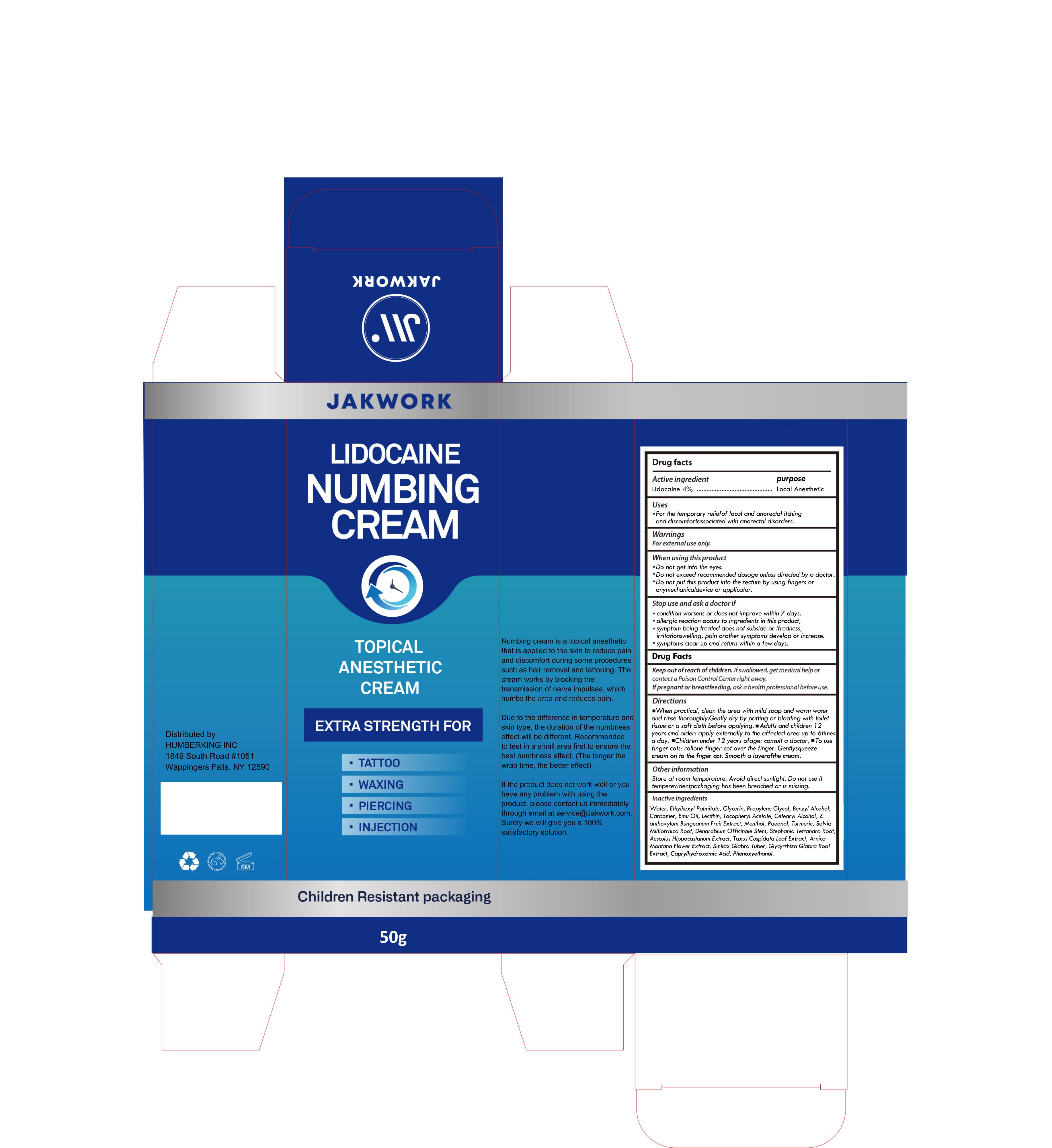 DRUG LABEL: Jakwork Numbing Cream
NDC: 85150-007 | Form: CREAM
Manufacturer: Guangzhou Zanming Trading Co., Ltd.
Category: otc | Type: HUMAN OTC DRUG LABEL
Date: 20250424

ACTIVE INGREDIENTS: LIDOCAINE 4 g/100 g
INACTIVE INGREDIENTS: SMILAX GLABRA TUBER; CAPRYLHYDROXAMIC ACID; GLYCERIN; CETEARYL ALCOHOL; WATER; ETHYLHEXYL PALMITATE; ZANTHOXYLUM BUNGEANUM FRUIT; BENZYL ALCOHOL; CARBOMER; PROPYLENE GLYCOL; .ALPHA.-TOCOPHEROL ACETATE; MENTHOL; TURMERIC; DENDROBIUM OFFICINALE STEM; STEPHANIA TETRANDRA ROOT; SALVIA MILTIORRHIZA ROOT; SOYBEAN OIL; GLYCYRRHIZA GLABRA WHOLE; PHENOXYETHANOL; EMU OIL; PAEONOL; AESCULUS HIPPOCASTANUM LEAF; TAXUS CUSPIDATA LEAF; ARNICA MONTANA

85150-007

Active Ingredient

Lidocaine 4%

Purpose

Local Anesthetic

Use

For the temporary relief of local and anorectal itching and discomfort associated with anorectal disorders.

Warnings

For external use only

Do not use

if packaging has been breached or is missing.

When Using

• Do not get into the eyes.
• Do not exceed recommended dosage unless directed by a doctor.
• Do not put this product into the rectum by using fingers or any mechanical device or applicator.

Stop Use

• condition worsens or does not improve within 7 days.
• allergic reaction occurs to ingredients in this product.
• symptom being treated does not subside or if redness, irritation swelling, pain or other symptoms develop or increase.
• symptoms clear up and return within a few days

Ask Doctor

if pregnant or breastfeeding

Keep Oot Of Reach Of Children

If swallowed, get medical help.

Directions

When practical, clean the area with mild soap and warm water and rinse thoroughly.
Gently dry by patting or bloating with toilet tissue or a soft cloth before applying.

a Adults and children 12 years and older: apply externally to the affected area up to 6 times a day. Children under 12 years of age: consult a doctor.

use finger cots: roll one finger cot over the finger. Gently squeeze cream on to the finger cot. Smooth a layer of the cream.

Other information

Store at room temperature. Avoid direct sunlight. Do not use if tamper-evident packaging has been breached or is missing.

Inactive ingredients

Water, Ethylhexyl Palmitate, Glycerin, Propylene Glycol, Benzyl Alcohol, Carbomer, Emu Oil, Lecithin, Tocopheryl Acetate, Cetyl Alcohol, Zanthoxylum Bungeanum Fruit Extract, Menthol, Paeonia Suffruticosa Root, Mentha Piperita Oil, Dendrobium Officinale Stem, Stephania Tetrandra Root, Aesculus Hippocastanum Extract, Taxus Cuspidata Leaf Extract, Arnica Montana Flower Extract, Smilax Glabra Tuber, Glycyrrhiza Glabra Root Extract, Caprylyl Glycol, Phenoxyethanol.